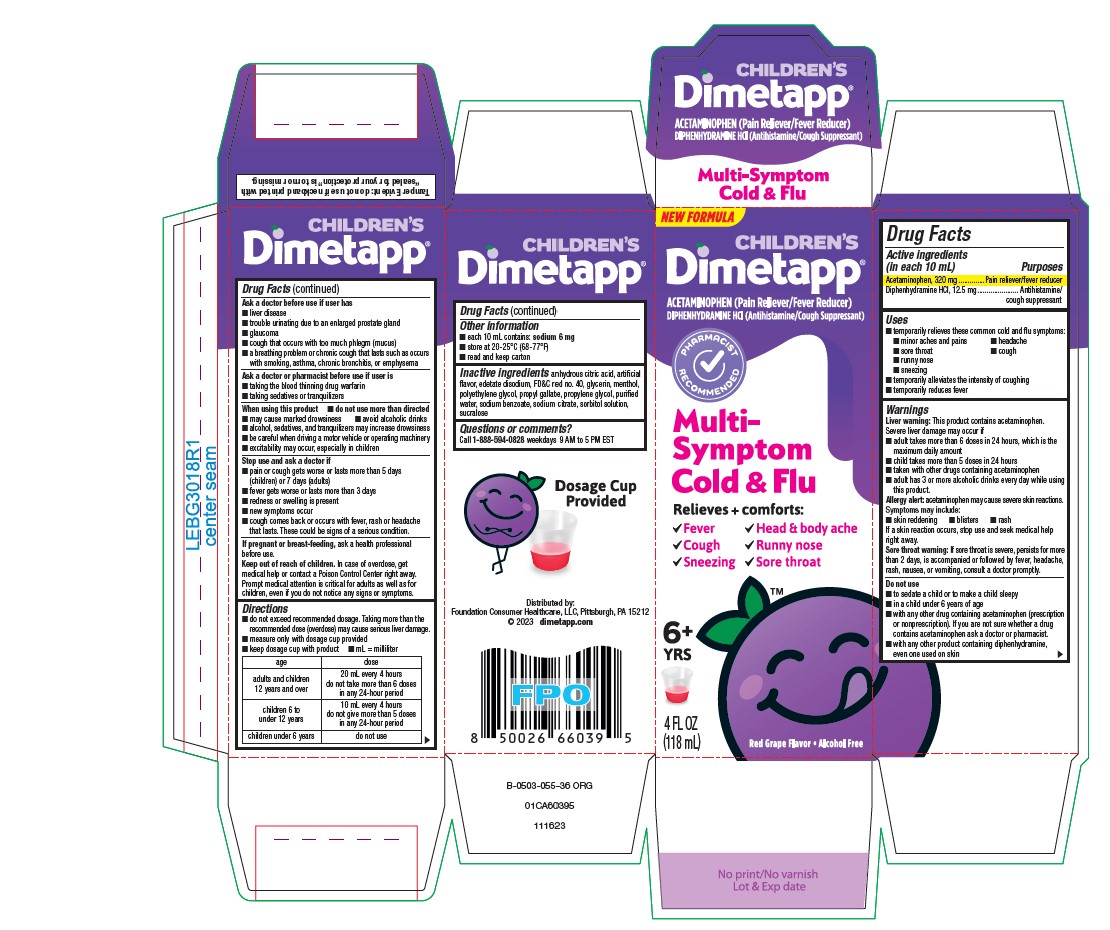 DRUG LABEL: Dimetapp
NDC: 69536-335 | Form: SOLUTION
Manufacturer: Foundation Consumer Healthcare
Category: otc | Type: HUMAN OTC DRUG LABEL
Date: 20251024

ACTIVE INGREDIENTS: ACETAMINOPHEN 320 mg/10 mL; DIPHENHYDRAMINE HYDROCHLORIDE 12.5 mg/10 mL
INACTIVE INGREDIENTS: ANHYDROUS CITRIC ACID; EDETATE DISODIUM; FD&C RED NO. 40; GLYCERIN; MENTHOL, UNSPECIFIED FORM; POLYETHYLENE GLYCOL, UNSPECIFIED; PROPYL GALLATE; PROPYLENE GLYCOL; WATER; SODIUM BENZOATE; SODIUM CITRATE, UNSPECIFIED FORM; SORBITOL; SUCRALOSE

Dimetapp®
Multi-Symptom Cold and Flu

Drug Facts

ACTIVE INGREDIENT

PURPOSE

Active ingredients (in each 10 mL) | Purposes
Acetaminophen, 320 mg | Pain reliever/fever reducer
Diphenhydramine HCl, 12.5 mg | Antihistamine/cough suppressant

Uses

- temporarily relieves these common cold and flu symptoms:
  - minor aches and pains
  - headache
  - sore throat
  - cough
  - runny nose
  - sneezing
  - temporarily alleviates the intensity of coughing
- temporarily reduces fever

Warnings

Liver warning

This product contains acetaminophen. Severe liver damage may occur if

- adult takes more than 6 doses in 24 hours, which is the maximum daily amount
- child takes more than 5 doses in 24 hours
- taken with other drugs containing acetaminophen
- adult has 3 or more alcoholic drinks every day while using this product.

Allergy alert:acetaminophen may cause severe skin reactions. Symptoms may include:

- skin reddening
- blisters
- rash

If a skin reaction occurs, stop use and seek medical help right away.

Sore throat warning

If sore throat is severe, persists for more than 2 days, is accompanied or followed by fever, headache, rash, nausea, or vomiting, consult a doctor promptly.

Do not use

- to sedate a child or to make a child sleepy
- in a child under 6 years of age
- with any other drug containing acetaminophen (prescription or nonprescription). If you are not sure whether a drug contains acetaminophen ask a doctor or pharmacist.
- with any other product containing diphenhydramine, even one used on skin

Ask a doctor before use if user has

- liver disease
- trouble urinating due to an enlarged prostate gland
- glaucoma
- cough that occurs with too much phlegm (mucus)
- a breathing problem or chronic cough that lasts or as occurs with smoking, asthma, chronic bronchitis, or emphysema

Ask a doctor or pharmacist before use if user is

- taking the blood thinning drug warfarin
- taking sedatives or tranquilizers

When using this product

- do not use more than directed
- may cause marked drowsiness
- avoid alcoholic drinks
- alcohol, sedatives, and tranquilizers may increase drowsiness
- be careful when driving a motor vehicle or operating machinery
- excitability may occur, especially in children

Stop use and ask a doctor if

- pain or cough gets worse or lasts more than 5 days (children) or 7 days (adults)
- fever gets worse or lasts more than 3 days
- redness or swelling is present
- new symptoms occur
- cough comes back or occurs with fever, rash or headache that lasts. These could be signs of a serious condition.

PREGNANCY OR BREAST FEEDING

If pregnant or breast-feeding, ask a health professional before use.

Keep out of reach of children. In case of overdose, get medical help or contact a Poison Control Center right away. Prompt medical attention is critical for adults as well as for children, even if you do not notice any signs or symptoms.

Directions

- do not exceed recommended dosage. Taking more than the recommended dose (overdose) may cause serious liver damage.
- measure only with dosage cup provided
- keep dosage cup with product
- mL = milliliter

age | dose
adults and children 12 years and over | 20 mL every 4 hours do not take more than 6 doses in any 24-hour period
children 6 to under 12 years | 10 mL every 4 hours do not give more than 5 doses in any 24-hour period
children under 6 years | do not use

Other information

- each 10 mL contains: sodium 6 mg
- store at 20-25°C (68-77°F)
- read and keep carton

Inactive ingredients

anhydrous citric acid, artificial flavor, edetate disodium, FD&C red no. 40, glycerin, menthol, polyethylene glycol, propyl gallate, propylene glycol, purified water, sodium benzoate, sodium citrate, sorbitol solution, sucralose

Questions or comments?

Call 1-888-594-0828 weekdays 9 AM to 5 PM EST

Distributed by:
Foundation Consumer Healthcare, LLC, Pittsburgh, PA 15212

PRINCIPAL DISPLAY PANEL - 118 mL Bottle Carton

NEW FORMULA

CHILDREN'S
Dimetapp®

ACETAMINOPHEN (Pain Reliever/Fever Reducer)
DIPHENHYDRAMINE HCl (Antihistamine/Cough Suppressant)

PHARMACIST
RECOMMENDED

Multi-
Symptom
Cold & Flu

Relieves + comforts:

- Fever
- Head & body aches
- Cough
- Runny nose
- Sneezing
- Sore throat

6+
YRS

4 FL OZ
(118 mL)

Red Grape Flavor • Alcohol Free